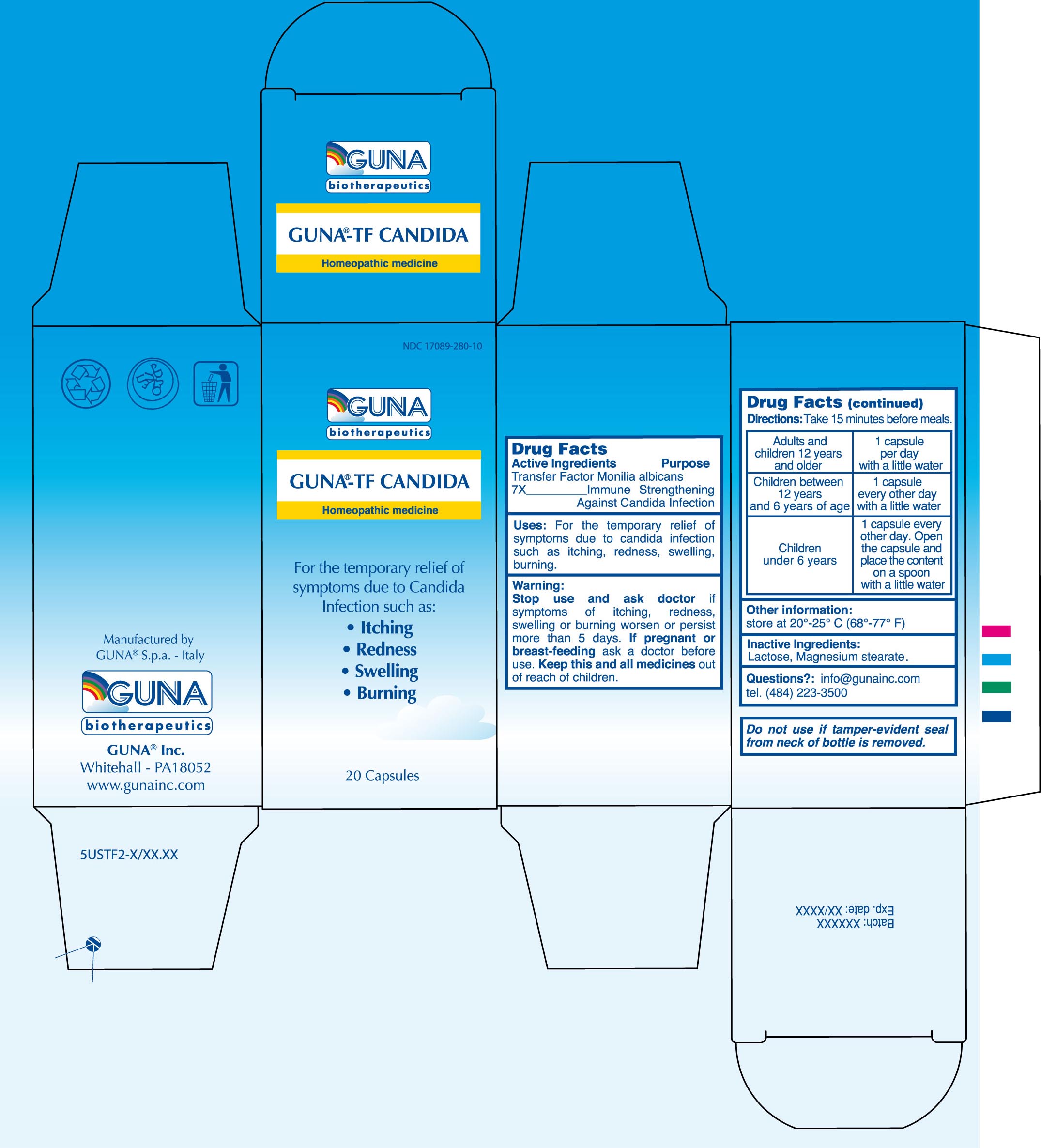 DRUG LABEL: GUNA-TF CANDIDA
NDC: 17089-280 | Form: CAPSULE, GELATIN COATED
Manufacturer: Guna spa
Category: homeopathic | Type: HUMAN OTC DRUG LABEL
Date: 20100324

ACTIVE INGREDIENTS: CANDIDA ALBICANS 7 [hp_X]/4600 mg
INACTIVE INGREDIENTS: LACTOSE 4048 mg/4600 mg; MAGNESIUM STEARATE 92 mg/4600 mg

DRUG FACTS

ACTIVE INGREDIENTS/PURPOSE

Transfer factor Monilia albicans 7x Immune strengthening against Candida infection

USES

For the temporary relief of symptoms due to Candida Infection such as: Itching, Redness, Swelling, Burning

WARNINGS

Stop use and ask doctor if symptoms of itching, redness, swelling or burning worsen or persist more than 5 days

PREGNANCY

If pregnant or breast-feeding ask a doctor before use

WARNINGS

Keep this and all medicines out of reach of children

DIRECTIONS

Take 15 minutes before meals
Adults and children 12 years and older 1 capsule per day with a little water
Children between 12 years and 6 years of age 1 capsule every other day, with a little water
Children under 6 years 1 capsule every other day. Open the capsule and place the content on a spoon with a little water

QUESTIONS

Questions?: info@gunainc.com
Tel. (484) 223-3500